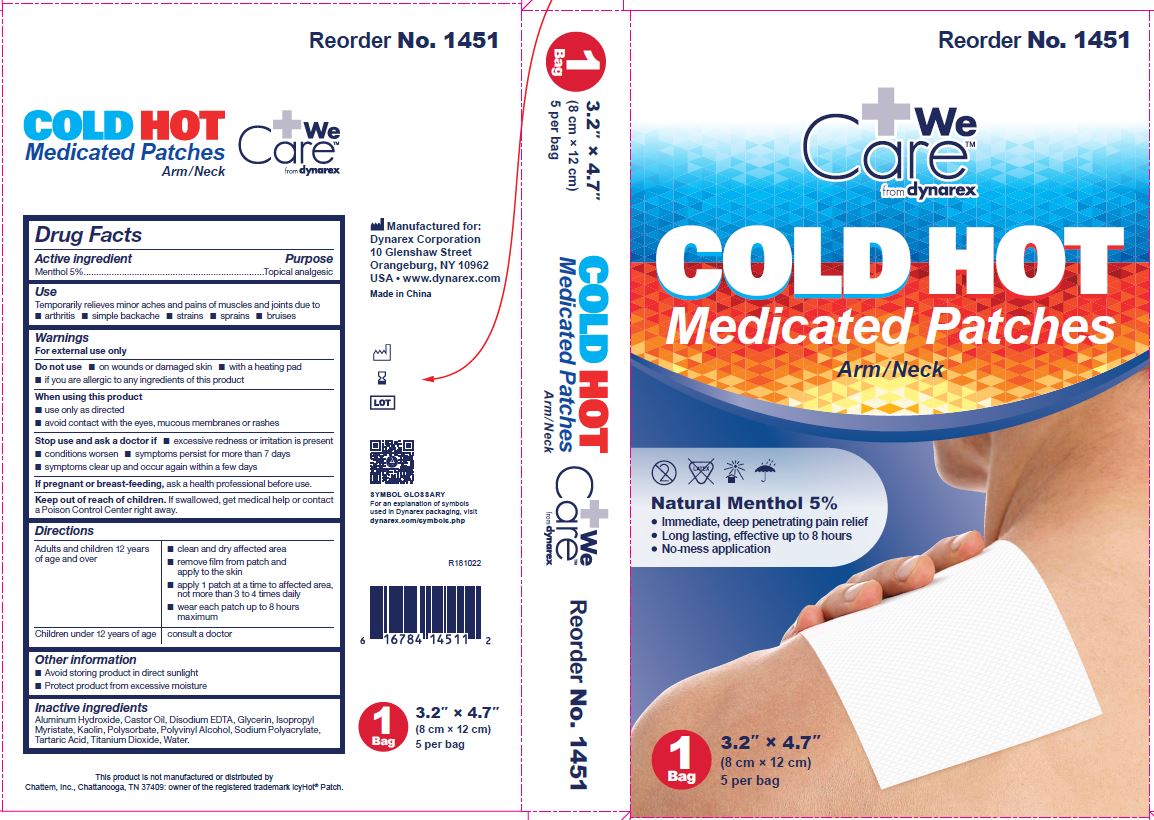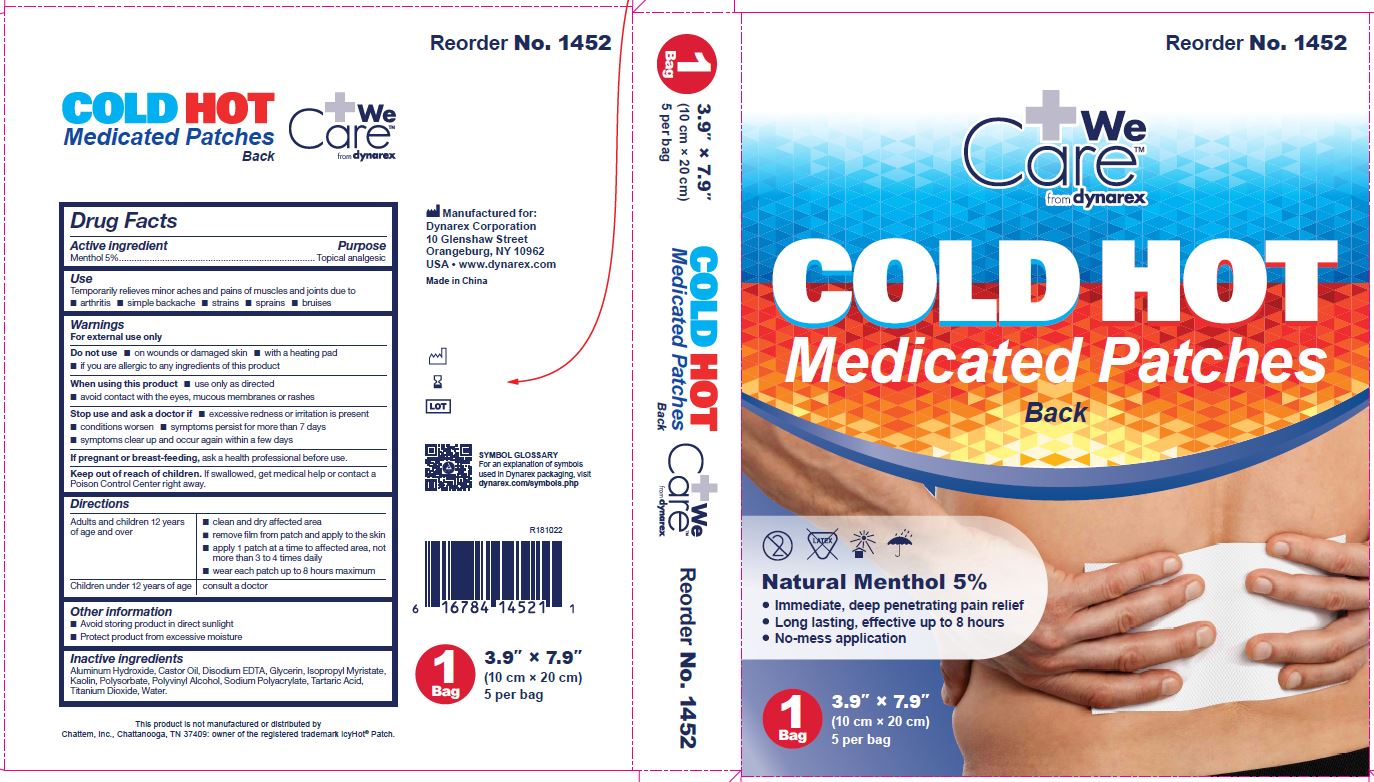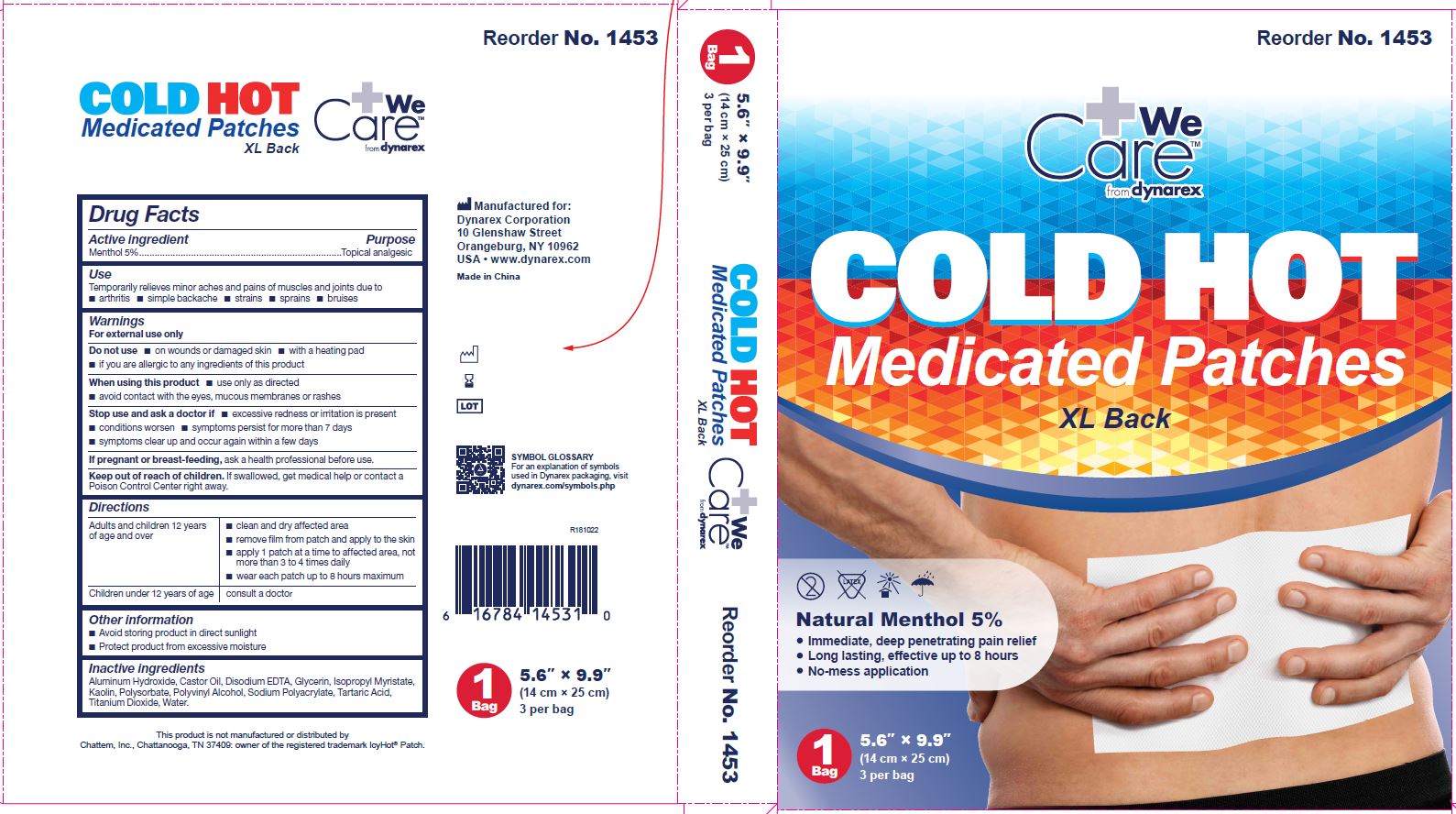 DRUG LABEL: Cold/Hot Medicated Patches
NDC: 67777-145 | Form: PATCH
Manufacturer: Dynarex Corporation
Category: otc | Type: HUMAN OTC DRUG LABEL
Date: 20181107

ACTIVE INGREDIENTS: MENTHOL 100 mg/5 mg
INACTIVE INGREDIENTS: EDETATE DISODIUM; ISOPROPYL MYRISTATE; POLYVINYL ALCOHOL, UNSPECIFIED; POLYSORBATE 80; TARTARIC ACID; GLYCERIN; SODIUM POLYACRYLATE (2500000 MW); ALUMINUM HYDROXIDE; TITANIUM DIOXIDE; WATER; CASTOR OIL; KAOLIN

1451 - NDC 67777-145-10
1452 - NDC 67777-145-20
1453 - NDC 67777-145-30

Active ingredient

Menthol 5%

Purpose

Topical analgesic

Use

Temporarily relieves minor aches and pains of muscles and joints due to arthritis, simple backache, strains, sprains, bruises

Warnings

For external use only

Do not use

on wounds or damaged skin, with a heating pad, if you are allergic to any ingredients of this product

When using this product

use only as directed, avoid contact with the eyes, mucous membranes or rashes

Stop use and ask a doctor if

- excessive redness or irritation is present
- conditions worsen
- symptoms persist for more than 7 days
- symptoms clear up and occur again within a few days

If pregnant or breast-feeding,

ask a health professional before use.

KEEP OUT OF REACH OF CHILDREN

If swallowed, get medical help or contact a Poison Control Center right away.

Directions

Adults and children 12 years of age and over

- clean and dry affected area
- remove film from patch and apply to the skin
- apply 1 patch at a time to affected area, not more than 3 to 4 times daily
- wear each patch up to 8 hours maximum

Children under 12 years of age

- consult a doctor

Other information

- Avoid storing product in direct sunlight
- Protect product from excessive moisture

Inactive ingredients

Aluminum Hydroxide, Castor Oil, Disodium EDTA, Glycerin, Isopropyl Myristate, Kaolin, Polysorbate, Polyvinyl Alcohol, Sodium Polyacrylate, Tartaric Acid, Titanium Dioxide, Water.